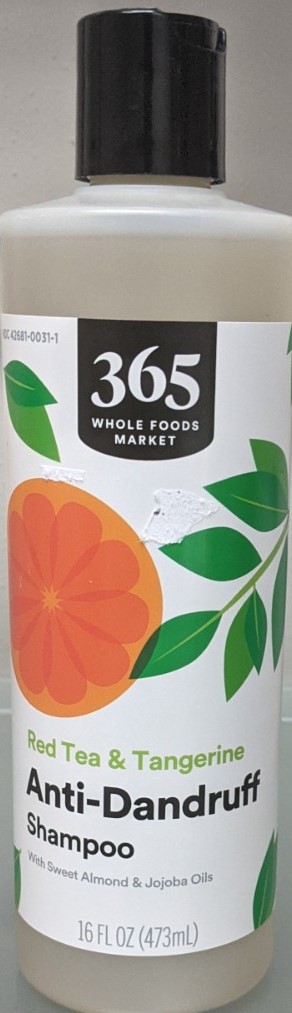 DRUG LABEL: AntiDandruffShampoo
NDC: 42681-0031 | Form: SHAMPOO
Manufacturer: Whole Foods Market, Inc.
Category: otc | Type: HUMAN OTC DRUG LABEL
Date: 20250429

ACTIVE INGREDIENTS: SALICYLIC ACID 30 mg/100 mL
INACTIVE INGREDIENTS: WATER 73 mL/100 mL

365 Anti-Dandruff Shampoo

Active Ingredients

Salicylic Acid 3% v/v

Purpose

Anti-Dandruff

Use

Helps prevent recurrence of flaking and itching associate with dandruff

Warnings

For external use only.

Avoid contact with eyes. If contact occurs, rinse eyes throughly with water

When using this product keep out of eyes. In case of contact with eyes, rinse eyes thoroughly with water. Stop use and ask doctor if irritation or rash occurs. These may be signs of a serious condition. Keep out of reach of children. If swallowed, get medical help or contact Poison Control Center right away.

Stop use and ask doctor if the condtion worsens or does not imporve after regular use of this product as directed.

Keep out of reach of children. If swallowed, get medical help or contact a Poison Control Center right away.

Directions

For best results use at least twice a week or as directed by a doctor. For maximum dandruff control, use every time you shampoo; shake before use; wet hair, massage onto scalp, rinse, repeat if desired.

Other information

Store in a cool dry place

Inactive Ingredients

Water, Sodium Coco-Sulfate, Cocamidopropyl Betaine, Glycerin, Aloe Barbadensis Leaf Juice, Gluconolactone, Fragrance, Decyl Glucoside, Phenoxyethanol, Benzyl Alcohol, Sodium Benzoate, Potassium Sorbate, Polyquaternium-7, Camellia Sinensis Leaf Extract, Hydrolyzed Quinoa, Simmondsia Chinensis (Jojoba) Seed Oil , Prunus Amygdalus Dulcis (Sweet Almond) Oil, Triethyl Citrate, Xylitol, Hydrolyzed Soy Protein.

Questions, Comments:

1-844-WFM-TALK (1-844-936-8255)